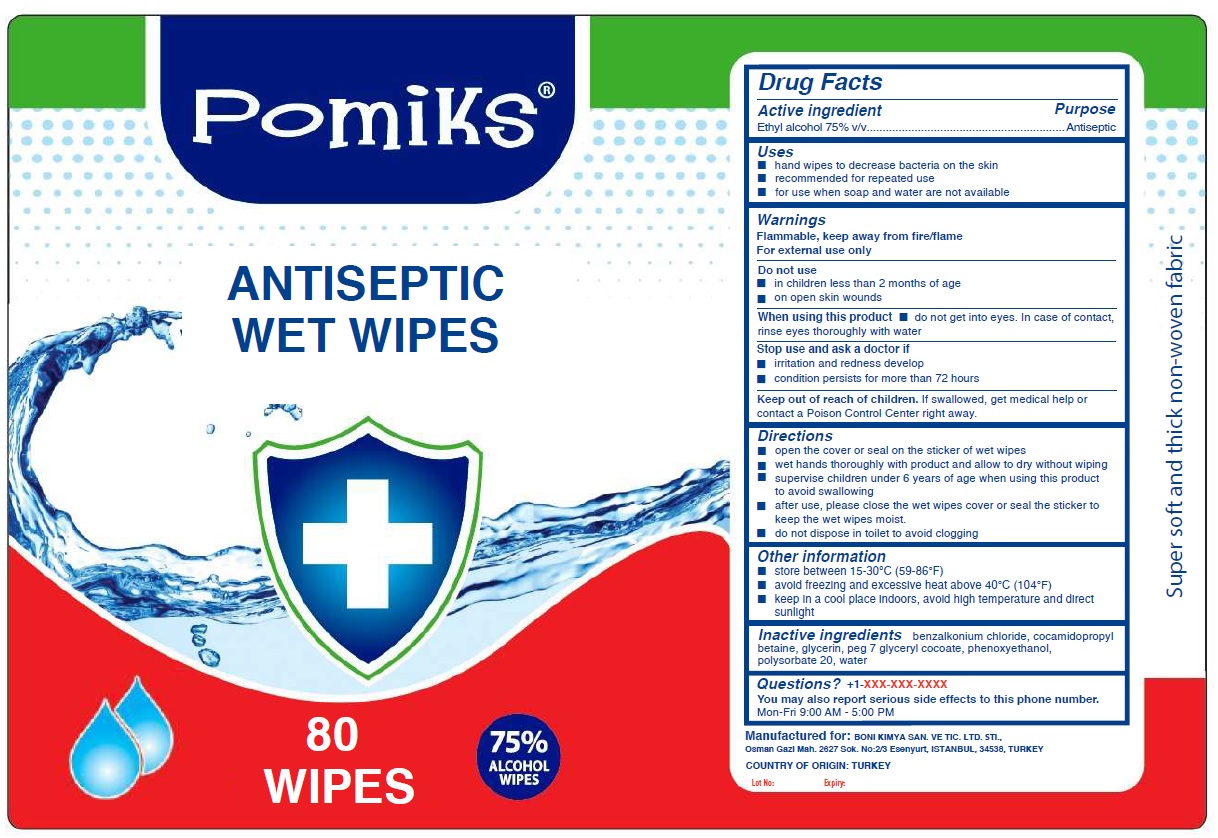 DRUG LABEL: Pomiks ANTISEPTIC WET WIPES
NDC: 81113-101 | Form: CLOTH
Manufacturer: BONI KIMYA SANAYI VE TICARET LIMITED SIRKETI
Category: otc | Type: HUMAN OTC DRUG LABEL
Date: 20201217

ACTIVE INGREDIENTS: ALCOHOL 75 mL/100 mL
INACTIVE INGREDIENTS: BENZALKONIUM CHLORIDE; COCAMIDOPROPYL BETAINE; GLYCERIN; PEG-7 GLYCERYL COCOATE; PHENOXYETHANOL; POLYSORBATE 20; WATER

Pomiks ® ANTISEPTIC WET WIPES

Active ingredient

Ethyl alcohol 75% v/v

Purpose

Antiseptic

Uses

- hand wipes to decrease bacteria on the skin
- recommended for repeated use
- for use when soap and water are not available

Warnings

Flammable, keep away from fire/flame
For external use only

Do not use

- in children less than 2 months of age
- on open skin wounds

When using this product • do not get into eyes. In case of contact, rinse eyes thoroughly with water

Stop use and ask a doctor if

- irritation and redness develop
- condition persists for more than 72 hours

Keep out of reach of children. If swallowed, get medical help or contact a Poison Control Center right away.

Directions

- open the cover or seal on the sticker of wet wipes
- wet hands thoroughly with product and allow to dry without wiping
- supervise children under 6 years of age when using this product to avoid swallowing
- after use, please close the wet wipes cover or seal the sticker to keep the wet wipes moist.
- do not dispose in toilet to avoid clogging

Other information

- store between 15-30°C (59-86°F)
- avoid freezing and excessive heat above 40°C (104°F)
- keep in a cool place indoors, avoid high temperature and direct sunlight

Inactive ingredients

benzalkonium chloride, cocamidopropyl betaine, glycerin, peg 7 glyceryl cocoate, phenoxyethanol, polysorbate 20, water

Questions? +1-XXX-XXX-XXXX

You may also report serious side effects to this phone number.

Mon-Fri 9:00 AM - 5:00 PM

75% ALCOHOL WIPES

Manufactured for: BONI KIMYA SAN. VE TIC. LTD. STI.,
Osman Gazi Mah. 2627 Sok. No:2/3 Esenyurt, ISTANBUL, 34538, TURKEY
COUNTRY OF ORIGIN: TURKEY

Super soft and thick non-woven fabric